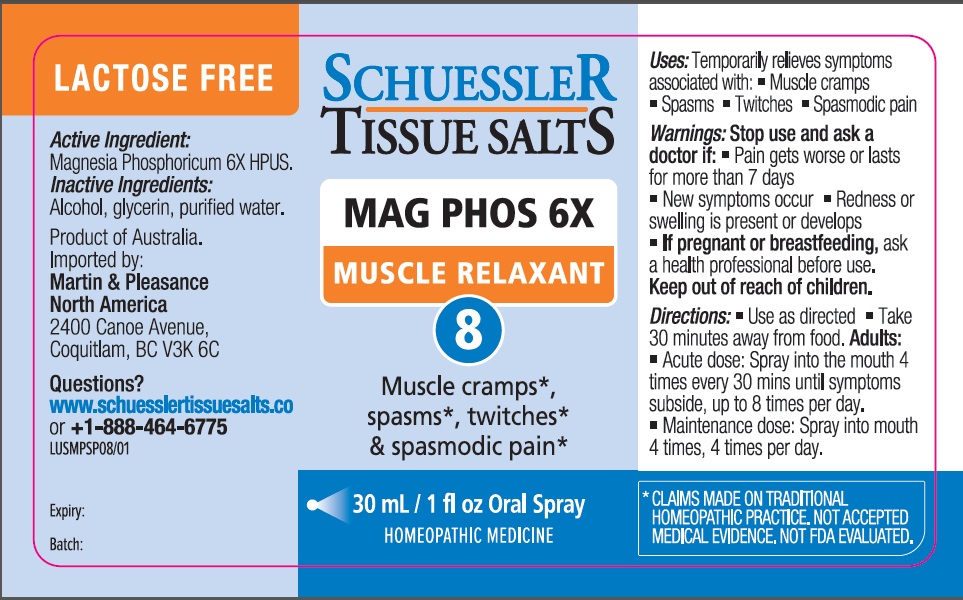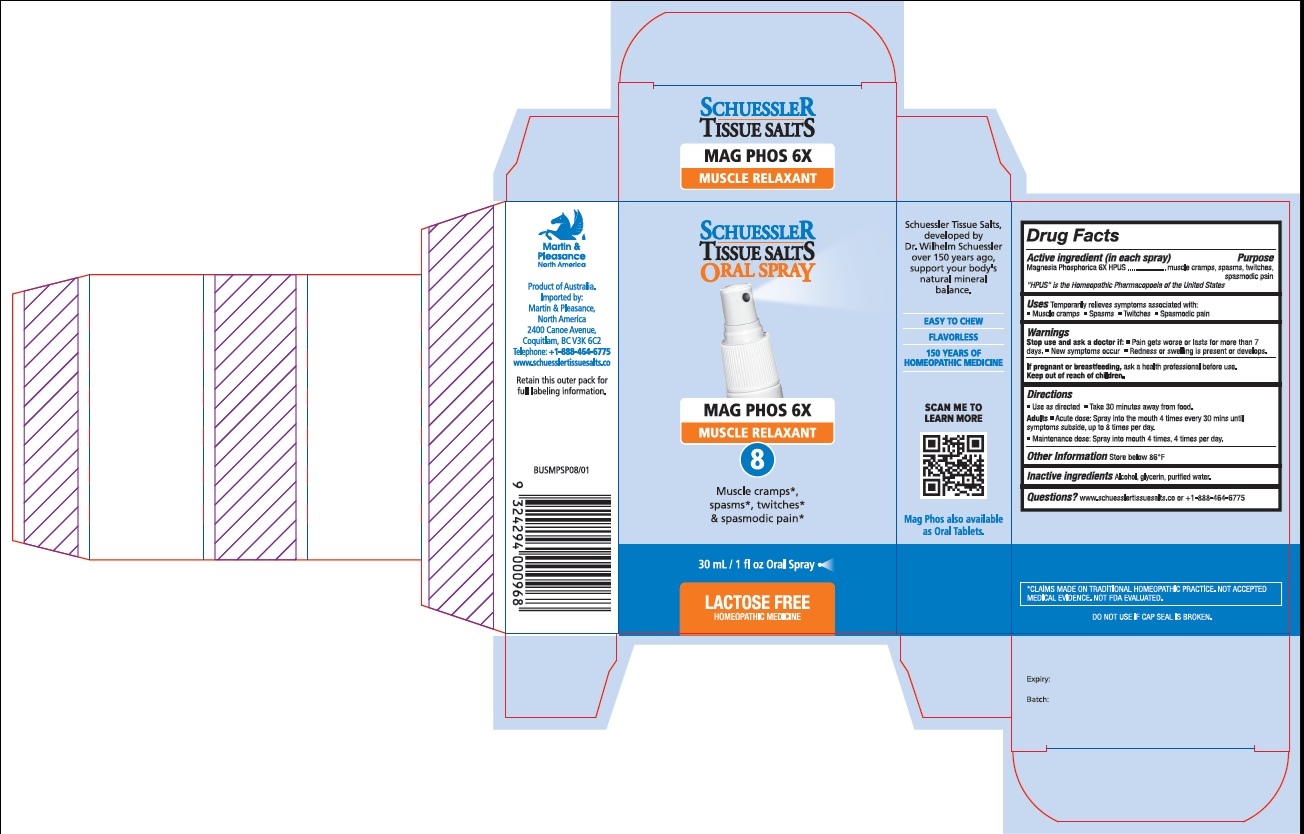 DRUG LABEL: Schuessler Tissue Salts Mag Phos Muscle Relaxant 8
NDC: 84999-008 | Form: SPRAY
Manufacturer: Martin & Pleasance Pty Ltd
Category: homeopathic | Type: HUMAN OTC DRUG LABEL
Date: 20250707

ACTIVE INGREDIENTS: MAGNESIUM PHOSPHATE, DIBASIC 6 [hp_X]/30 mL
INACTIVE INGREDIENTS: ALCOHOL; GLYCERIN; WATER

Active ingredient (in each spray) Purpose

Magnesia Phosphorica 6X HPUS muscle cramps, spasms, twitches,spasmodic pain

“ HPUS” is the Homeopathic Pharmacopoeia of the United States

Uses

Temporarily relieves symptoms associated with:

• Muscle cramps

• Spasms

• Twitches

• Spasmodic pain

Warnings

Stop use and ask a doctor if:

- Pain gets worse or lasts for more than 7 days.
- New symptoms occur
- Redness or swelling is present or develops.

If pregnant or breastfeeding, ask a health professional before use. Keep out of reach of children.

Directions

- Use as directed
- Take 30 minutes away from food.

Adults

- Acute dose: Spray into the mouth 4 times every 30 mins until symptoms subside, up to 8 times per day.
- Maintenance dose: Spray into mouth 4 times, 4 times per day.

Other Information

Store below 86°F.

Inactive Ingredients

Alcohol, Glycerin, Purified Water

Questions?www.schuesslertissuesalts.co or + 1-888-464-6775